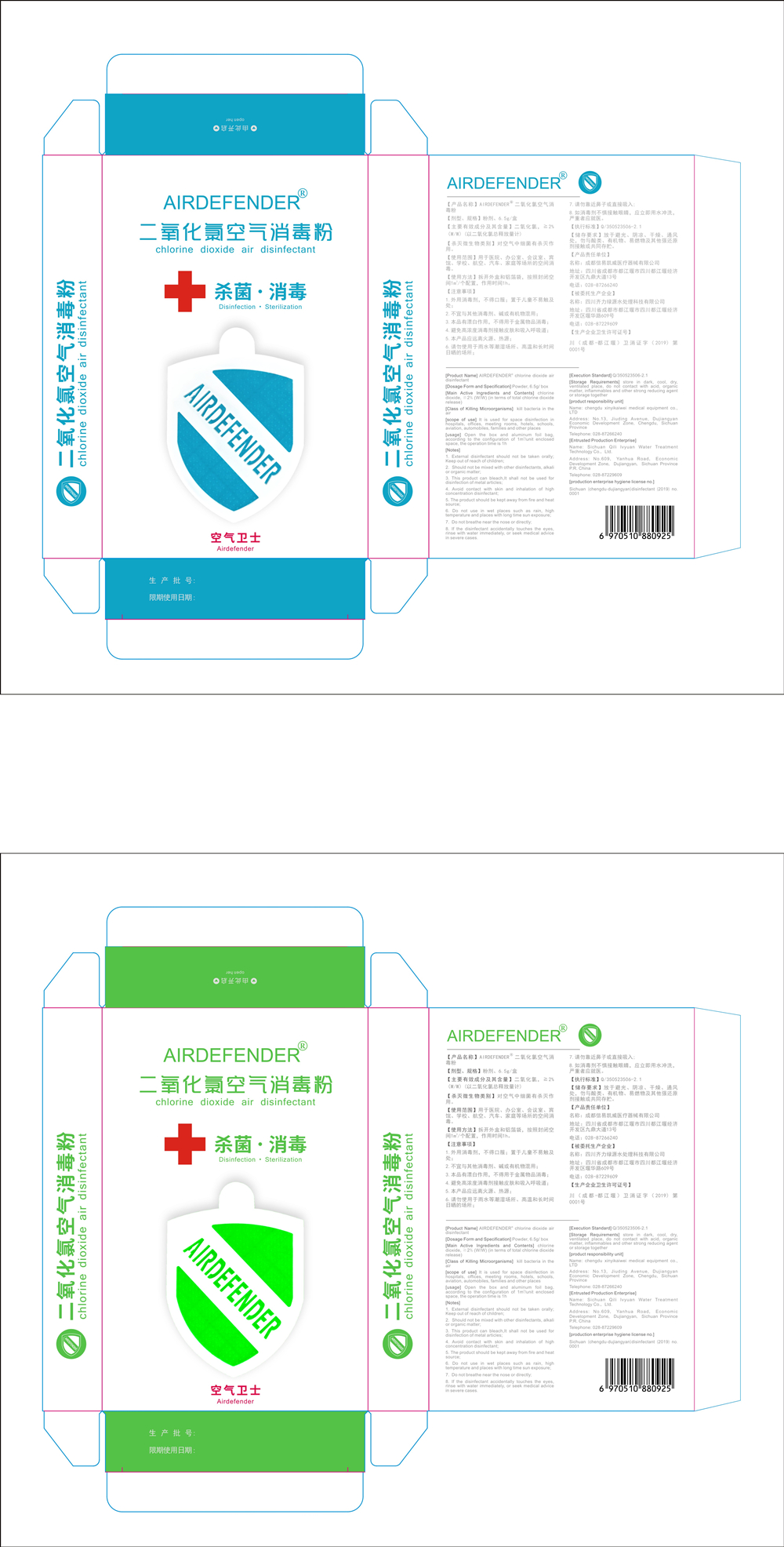 DRUG LABEL: chlorine dioxide air disinfectant
NDC: 55090-001 | Form: POWDER
Manufacturer: Chengdu Xinyi Kaiwei Medical Equipment Co., Ltd.
Category: otc | Type: HUMAN OTC DRUG LABEL
Date: 20200506

ACTIVE INGREDIENTS: CHLORINE DIOXIDE 130 mg/6.5 g
INACTIVE INGREDIENTS: CALCIUM CHLORIDE; SODIUM BISULFATE; SODIUM SULFATE ANHYDROUS; SODIUM CHLORITE

DOSAGE AND ADMINISTRATION

store in dark, cool, dry,ventilated_ place, do not contact with acid, organic matter, inflammables and other strong reducing agent or storage together

INACTIVE INGREDIENT

Anhydrous sodium sulfate

Calciun chloride

Sodium bisulfate

Sodium chlorite

INDICATIONS AND USAGE

Open the box and aluminum foil bag,according to the configuration of 1m/unit enclosed space, the operation time is 1h

ACTIVE INGREDIENT

Chlorine Dioxide

keep out of reach of children

PURPOSE

Disinfection
Sterilization

WARNINGS

1. External disinfectant should not be taken orally;Keep out of reach of children;
2. Should not be mixed with other disinfectants, alkali or organic matter;
3. This product can bleach,It shall not be used for disinfection of metal articles;
4. Avoid contact with skin and inhalation of high concentration disinfectant;
5. The product should be kept away from fire and heat source;
6. Do not use in wet places such as rain, high temperature and places with long time sun exposure;
7. Do not breathe near the nose or directly;
8. If the. disinfectant accidentally touches. the eyes,rinse with water immediately, or seek medical advice in severe cases.